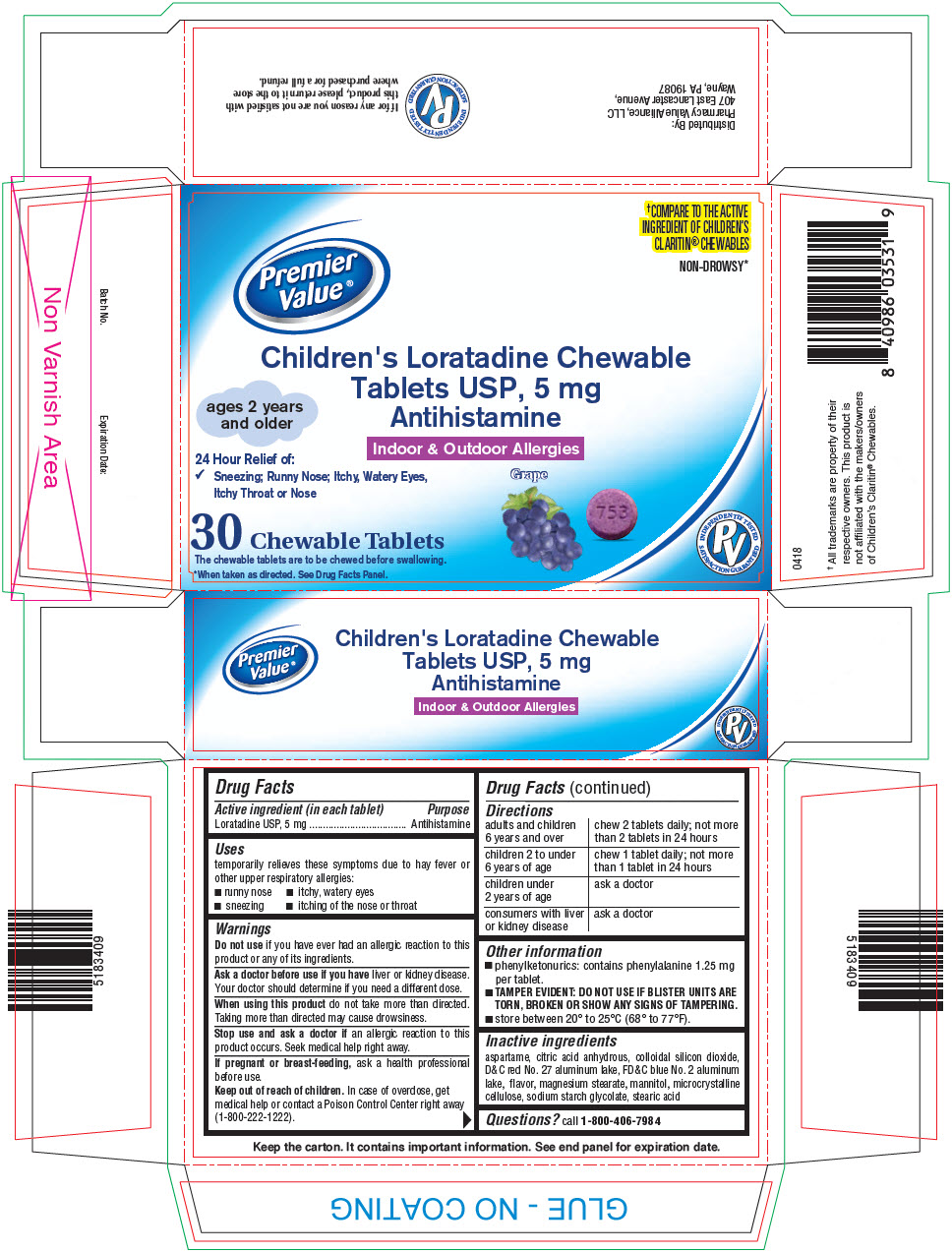 DRUG LABEL: Loratadine
NDC: 68016-053 | Form: TABLET
Manufacturer: Premier Value
Category: otc | Type: HUMAN OTC DRUG LABEL
Date: 20241227

ACTIVE INGREDIENTS: LORATADINE 5 mg/1 1
INACTIVE INGREDIENTS: ASPARTAME; ANHYDROUS CITRIC ACID; SILICON DIOXIDE; D&C RED NO. 27 ALUMINUM LAKE; FD&C BLUE NO. 2--ALUMINUM LAKE; MAGNESIUM STEARATE; MANNITOL; MICROCRYSTALLINE CELLULOSE; SODIUM STARCH GLYCOLATE TYPE A POTATO; STEARIC ACID

Loratadine

Drug Facts

Active ingredient (in each tablet)

Loratadine USP, 5 mg

Purpose

Antihistamine

Uses

temporarily relieves these symptoms due to hay fever or other upper respiratory allergies:

- runny nose
- itchy, watery eyes
- sneezing
- itching of the nose or throat

Warnings

DO NOT USE

Do not useif you have ever had an allergic reaction to this product or any of its ingredients.

Ask a doctor before use if you haveliver or kidney disease. Your doctor should determine if you need a different dose.

WHEN USING

When using this productdo not take more than directed. Taking more than directed may cause drowsiness.

Stop use and ask a doctor ifan allergic reaction to this product occurs. Seek medical help right away.

PREGNANCY OR BREAST FEEDING

If pregnant or breast-feeding,ask a health professional before use.

Keep out of reach of children.In case of overdose, get medical help or contact a Poison Control Center right away (1-800-222-1222).

Directions

adults and children 6 years and over | chew 2 tablets daily; not more than 2 tablets in 24 hours
children 2 to under 6 years of age | chew 1 tablet daily; not more than 1 tablet in 24 hours
children under 2 years of age | ask a doctor
consumers with liver or kidney disease | ask a doctor

Other information

- phenylketonurics: contains phenylalanine 1.25 mg per tablet.
- TAMPER EVIDENT: DO NOT USE IF BLISTER UNITS ARE TORN, BROKEN OR SHOW ANY SIGNS OF TAMPERING.
- store between 20° to 25°C (68° to 77°F).

Inactive ingredients

aspartame, citric acid anhydrous, colloidal silicon dioxide, D&C red No. 27 aluminum lake, FD&C blue No. 2 aluminum lake, flavor, magnesium stearate, mannitol, microcrystalline cellulose, sodium starch glycolate, stearic acid

Questions?

call 1-800-406-7984

Distributed By:
Pharmacy Value Alliance, LLC
407 East Lancaster Avenue,
Wayne, PA 19087

PRINCIPAL DISPLAY PANEL - 5 mg Blister Pack Carton

†COMPARE TO THE ACTIVE
INGREDIENT OF CHILDREN'S
CLARITIN®CHEWABLES
NON-DROWSY*

Premier
Value®

Children's Loratadine Chewable
Tablets USP, 5 mg
Antihistamine

Indoor & Outdoor Allergies

Grape

ages 2 years
and older

24 Hour Relief of:

- Sneezing; Runny Nose; Itchy, Watery Eyes,
  Itchy Throat or Nose

30 Chewable Tablets
The chewable tablets are to be chewed before swallowing.
*When taken as directed. See Drug Facts Panel.

INDEPENDENTLY TESTED
SATISFACTION GUARANTEED